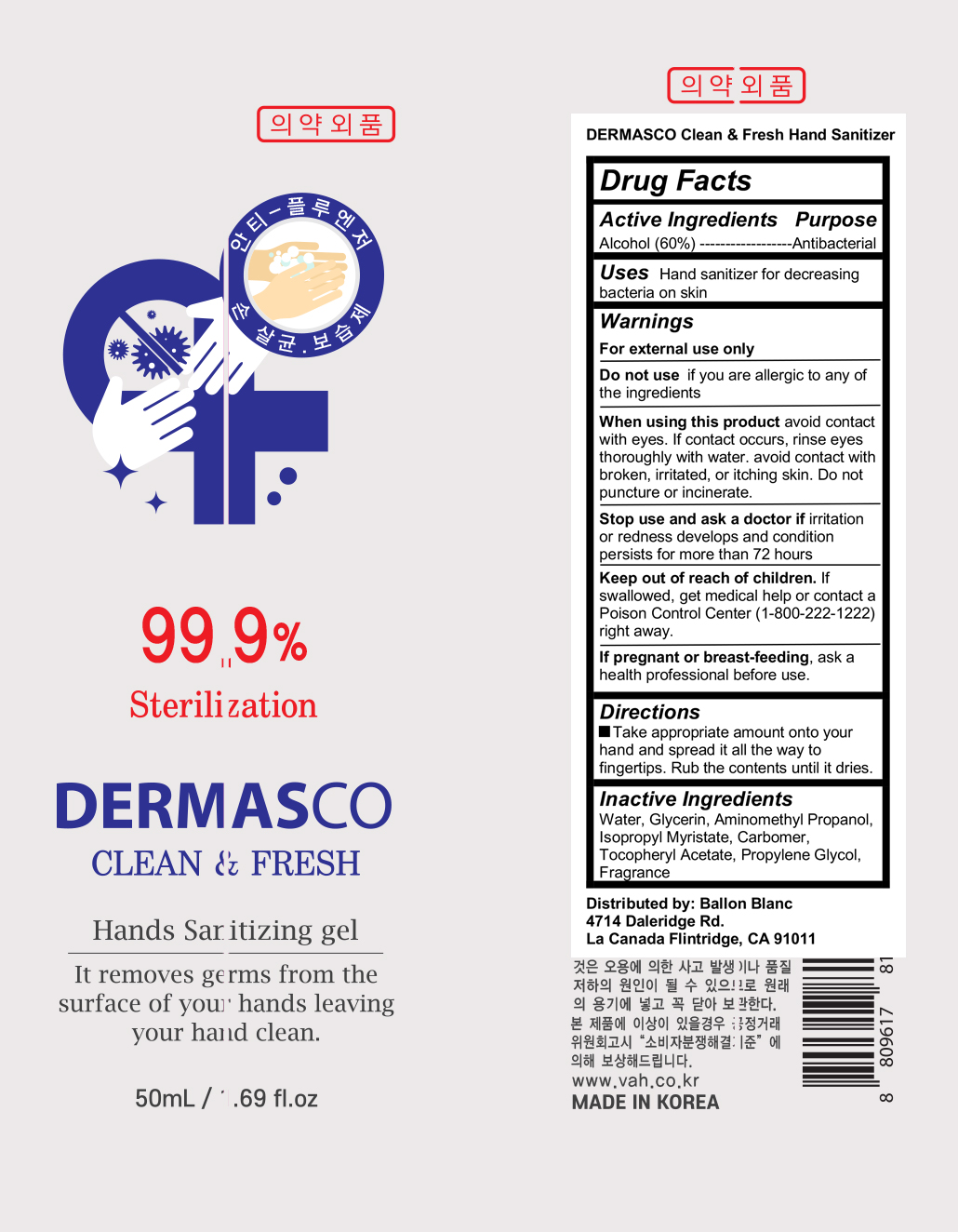 DRUG LABEL: DERMASCO Clean and Fresh Hands Sanitizing
NDC: 74187-100 | Form: GEL
Manufacturer: VAH CO., LTD
Category: otc | Type: HUMAN OTC DRUG LABEL
Date: 20220111

ACTIVE INGREDIENTS: ALCOHOL 30 g/50 mL
INACTIVE INGREDIENTS: ISOPROPYL MYRISTATE; GLYCERIN; AMINOMETHYLPROPANOL; WATER; CARBOMER HOMOPOLYMER, UNSPECIFIED TYPE; PROPYLENE GLYCOL; .ALPHA.-TOCOPHEROL ACETATE

DERMASCO Clean & Fresh Hands Sanitizing Gel

Active ingredient

Alcohol (60%)

Uses

Hand sanitizer for decreasing bacteria on skin

Purpose

Antibacterial

Warnings

For external use only

Do not use if you are allergic to any of the ingredients

When using this product avoid contact with eyes. If contact occurs, rinse eyes thoroughly with water. avoid contact with broken, irritated, or itching skin. Do not puncture or incinerate.

Stop use and ask a doctor if irritation or redness develops and condition persists for more than 72 hours

If pregnant or breast-feeding, ask a health professional before use.

Directions

Take appropriate amount onto your hand and spread it all the way to fingertips. Rub the contents until it dries

Inactive ingredients

Water, Glycerin, Aminomethyl Propanol, Isopropyl Myristate, Carbomer, Tocopheryl Acetate, Propylene Glycol, Fragrance

Keep out of reach of children. If swallowed, get medical help or contact a Poison Control Center (1-800-222-1222) right away.